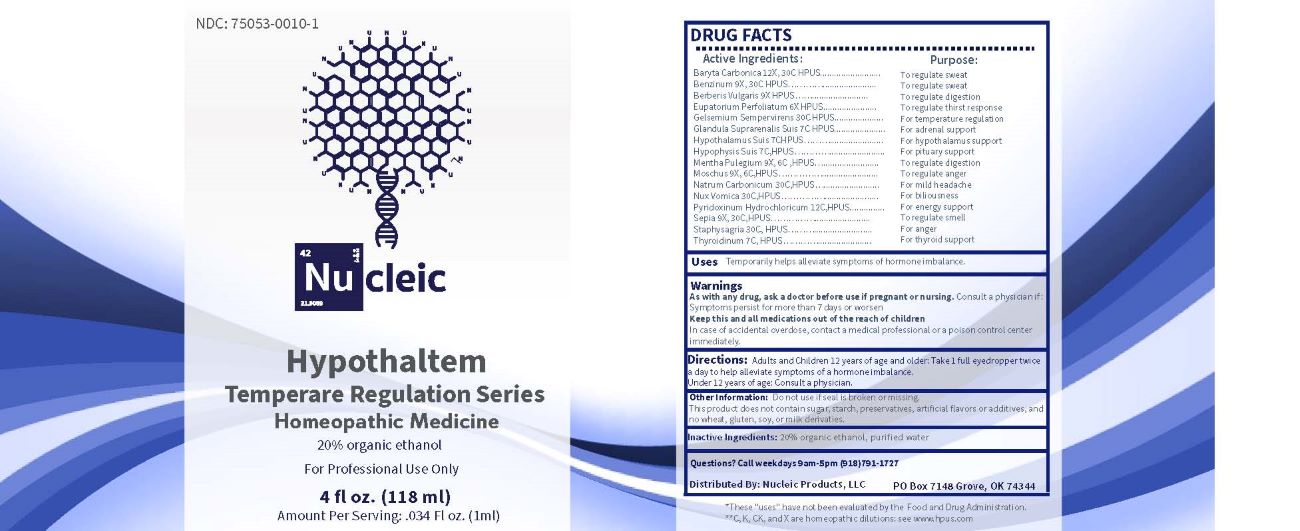 DRUG LABEL: Hypothaltem
NDC: 75053-0010 | Form: LIQUID
Manufacturer: Nucleic Products, LLC
Category: homeopathic | Type: HUMAN OTC DRUG LABEL
Date: 20250320

ACTIVE INGREDIENTS: EUPATORIUM PERFOLIATUM FLOWERING TOP 6 [hp_X]/1 mL; BERBERIS VULGARIS ROOT BARK 9 [hp_X]/1 mL; MENTHA PULEGIUM WHOLE 9 [hp_X]/1 mL; MOSCHUS MOSCHIFERUS MUSK SAC RESIN 9 [hp_X]/1 mL; BENZENE 9 [hp_X]/1 mL; SEPIA OFFICINALIS JUICE 9 [hp_X]/1 mL; BARIUM CARBONATE 12 [hp_X]/1 mL; SUS SCROFA ADRENAL GLAND 7 [hp_C]/1 mL; SUS SCROFA PITUITARY GLAND 7 [hp_C]/1 mL; SUS SCROFA HYPOTHALAMUS 7 [hp_C]/1 mL; THYROID, UNSPECIFIED 7 [hp_C]/1 mL; PYRIDOXINE HYDROCHLORIDE 12 [hp_C]/1 mL; GELSEMIUM SEMPERVIRENS ROOT 30 [hp_C]/1 mL; SODIUM CARBONATE 30 [hp_C]/1 mL; STRYCHNOS NUX-VOMICA SEED 30 [hp_C]/1 mL; DELPHINIUM STAPHISAGRIA SEED 30 [hp_C]/1 mL
INACTIVE INGREDIENTS: WATER; ALCOHOL

DRUG FACTS:

ACTIVE INGREDIENTS:

Baryta Carbonica 12X , 30C HPUS, Benzinum 9X, 30C HPUS, Berberis Vulgaris 9X HPUS, Eupatorium Perfoliatum 6X HPUS, Gelsemium Sempervirens 30C HPUS, Glandula Suprarenalis Suis 7C HPUS, Hypothalamus Suis 7C HPUS, Hypophysis Suis 7C HPUS, Mentha Pulegium 9X, 6C HPUS, Moschus 9X, 6C HPUS, Natrum Carbonicum 30C HPUS, Nux Vomica 30C HPUS, Pyridoxinum Hydrochloricum 12C HPUS, Sepia 9X, 30C HPUS, Staphysagria 30C HPUS, Thyroidinum 7C HPUS.

PURPOSE:

Baryta Carbonica – To regulate sweat, Benzinum – To regulate sweat, Berberis Vulgaris – To regulate digestion, Eupatorium Perfoliatum – To regulate thirst response, Gelsemium Sempervirens – For temperature regulation, Glandula Suprarenalis Suis – For adrenal support, Hypothalamus Suis – For hypothalamus support, Hypophysis Suis – For pituitary support, Mentha Pulegium – To regulate digestion, Moschus – To regulate anger, Natrum Carbonicum – For mild headache, Nux Vomica – For biliousness, Pyridoxinum Hydrochloricum – For energy support, Sepia – To regulate smell, Staphysagria – For anger, Thyroidinum – For thyroid support

USES:

Temporarily helps alleviate symptoms of hormone imbalance.*
*These “uses” have not been evaluated by the Food and Drug Administration.

WARNINGS:

As with any drug, ask a doctor before use if pregnant or nursing. Consult a physician if Symptoms persist for more than 7 days or worsen.
Keep this and all medications out of the reach of children
In case of accidental overdose, contact a medical professional or a poison control center immediately.
Do not use if seal is broken or missing.
This product does not contain sugar, starch, preservatives, artificial flavors or additives, and no wheat, gluten , soy, or milk derivatives.

KEEP OUT OF REACH OF CHILDREN:

In case of accidental overdose, contact a medical professional or a poison control center immediately.

DIRECTIONS:

Adults and Children 12 years of age and older: Take 1 full eyedropper twice a day to help alleviate symptoms of a hormone imbalance.
Under 12 years of age: Consult a physician.

INACTIVE INGREDIENTS

20% organic ethanol, purified water

QUESTIONS:

Distributed by: Nucleic Products, LLC

PO Box 7148 Grove, OK 74344

(918) 791-1727

PACKAGE LABEL DISPLAY:

NDC: 75053-0010-1

Nu cleic

Hypothaltem

Homeopathic Medicine

For Professional Use Only

4 fl oz. (118 ml)